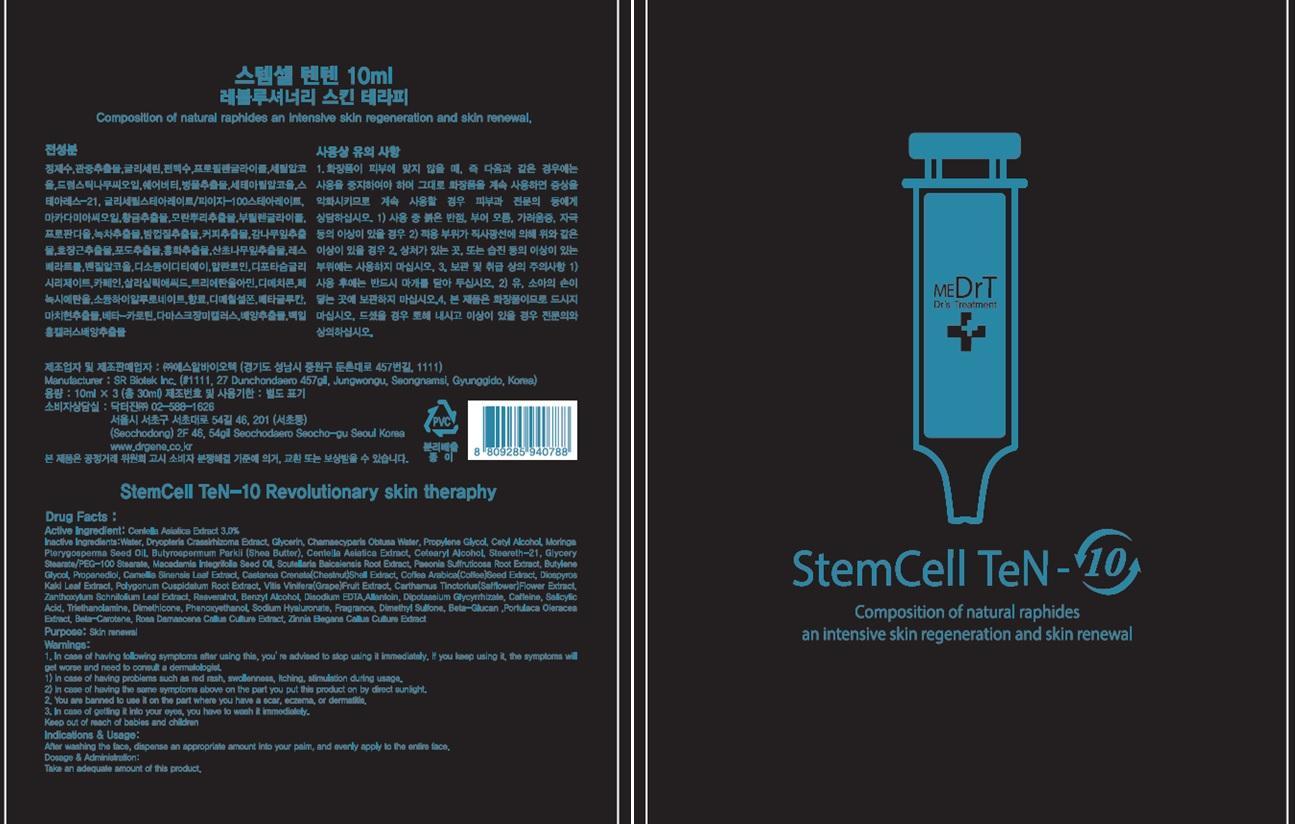 DRUG LABEL: StemCell TeN 10
NDC: 69783-010 | Form: CREAM
Manufacturer: Dr.Gene Co.,Ltd
Category: otc | Type: HUMAN OTC DRUG LABEL
Date: 20150602

ACTIVE INGREDIENTS: CENTELLA ASIATICA 0.3 mg/3 1
INACTIVE INGREDIENTS: Water; Glycerin

ACTIVE INGREDIENT

Active Ingredient: Centella Asiatica Extract 3.0%

INACTIVE INGREDIENT

Inactive Ingredients: Water, Dryopteris Crassirhizoma Extract, Glycerin, Chamaecyparis Obtusa Water, Propylene Glycol, Cetyl Alcohol, Moringa Pterygosperma Seed Oil, Butyrospermum Parkii (Shea Butter), Centella Asiatica Extract, Cetearyl Alcohol, Steareth-21, Glycery Stearate/PEG-100 Stearate, Macadamia Integrifolia Seed Oil, Scutellaria Baicalensis Root Extract, Paeonia Suffruticosa Root Extract, Butylene Glycol, Propanediol, Camellia Sinensis Leaf Extract, Castanea Crenata(Chestnut)Shell Extract, Coffea Arabica(Coffee)Seed Extract, Diospyros Kaki Leaf Extract, Polygonum Cuspidatum Root Extract, Vitis Vinifera(Grape)Fruit Extract, Carthamus Tinctorius(Safflower)Flower Extract, Zanthoxylum Schnifolium Leaf Extract, Resveratrol, Benzyl Alcohol, Disodium EDTA,Allantoin, Dipotassium Glycyrrhizate, Caffeine, Salicylic Acid, Triethanolamine, Dimethicone, Phenoxyethanol, Sodium Hyaluronate, Fragrance, Dimethyl Sulfone, Beta-Glucan ,Portulaca Oleracea Extract, Beta-Carotene, Rosa Damascena Callus Culture Extract, Zinnia Elegans Callus Culture Extract

PURPOSE

Purpose: Skin renewal

WARNINGS

Warnings: 1. In case of having following symptoms after using this, you’re advised to stop using it immediately. If you keep using it, the symptoms will get worse and need to consult a dermatologist. 1) In case of having problems such as red rash, swollenness, itching, stimulation during usage. 2) In case of having the same symptoms above on the part you put this product on by direct sunlight. 2. You are banned to use it on the part where you have a scar, eczema, or dermatitis. 3. In case of getting it into your eyes, you have to wash it immediately.

Keep out of reach of children: Keep out of reach of babies and children

INDICATIONS & USAGE

Indications & Usage: After washing the face, dispense an appropriate amount into your palm, and evenly apply to the entire face.

DOSAGE & ADMINISTRATION

Dosage & Administration: Take an adequate amount of this product.